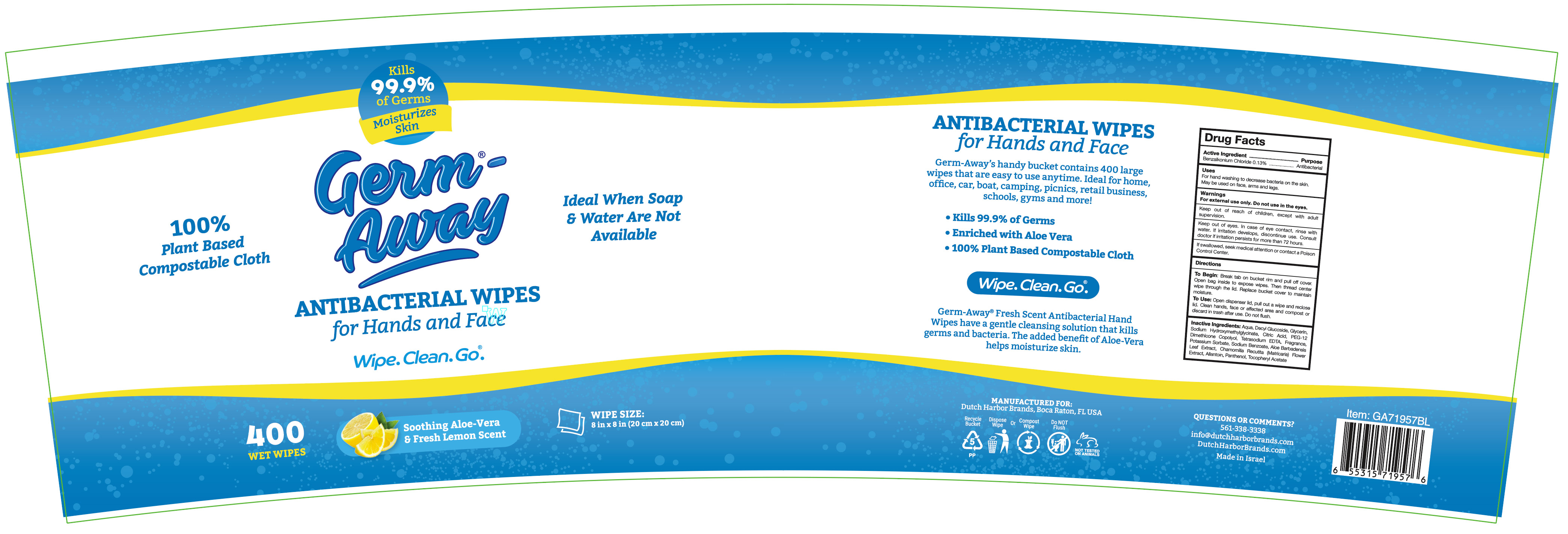 DRUG LABEL: Germ-Away
NDC: 74680-103 | Form: CLOTH
Manufacturer: Unico International Trading Corp
Category: otc | Type: HUMAN OTC DRUG LABEL
Date: 20260108

ACTIVE INGREDIENTS: BENZALKONIUM CHLORIDE 1.3 mg/1 g
INACTIVE INGREDIENTS: EUCALYPTOL; COUMARIN; DIPHENYL ETHER; ALOE VERA LEAF; CP FORMATE; 2,2'-OXYDIPROPANOL; ANHYDROUS CITRIC ACID; CHAMOMILE; DECYL GLUCOSIDE; TETRAHYDROLINALOOL; WATER; .ALPHA.-TOCOPHEROL ACETATE; POTASSIUM SORBATE; EDETATE SODIUM; ALLANTOIN; GLYCERIN; PEG-12 DIMETHICONE (300 CST); SODIUM HYDROXYMETHYLGLYCINATE; SODIUM BENZOATE; PANTHENOL; 3,7-DIMETHYL-1-OCTANOL

Germ-Away

Active Ingredient

Benzalkonium chloride 0.1%

Purpose

Anti-bacterial

Keep out of the reach of children

Keep out of reach of children, except with adult supervision.

Warnings

For external use only. Do not use in the eyes.

Keep out of eyes. In case of eye contact, rinse with water. If irritation develops, discontinue use. Consult doctor if irritation persists for more than 72 hours.

If swallowed, seek medical attention or contact a Poison Control Center.

Directions

Pull one sheet from pack. Sanitize hands or other affected area. Discard in trash after use. Do not flush. Close tab after use to retain moisture.

Inactive Ingredients

Aqua, Decyl Glucoside, Glycerin, Sodium Hydroxymethylglycinate, Citric Acid, PEG-12 Dimethicone Copolyol, Tetrasodium EDTA, Potassium Sorbate, Sodium Benzoate, Aloe Barbadensis Leaf Extract, Chamomilla Recutita (Matricaria) Flower Extract, Allantoin, Panthenol, Tocopheryl Acetate, Fragrance

To Use

Break tab on bucket rim and pull off cover. Open bag inside to expose wipes. Then thread center wipe through the lid. Replace bucket cover to maintain moisture.